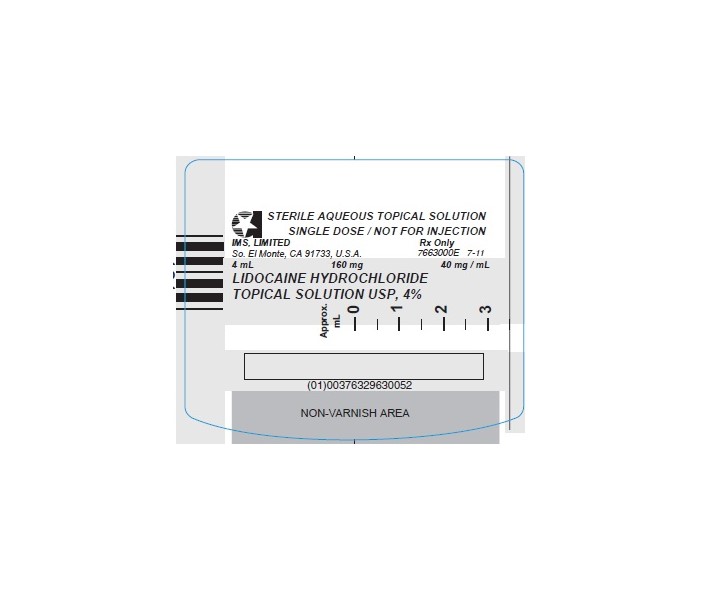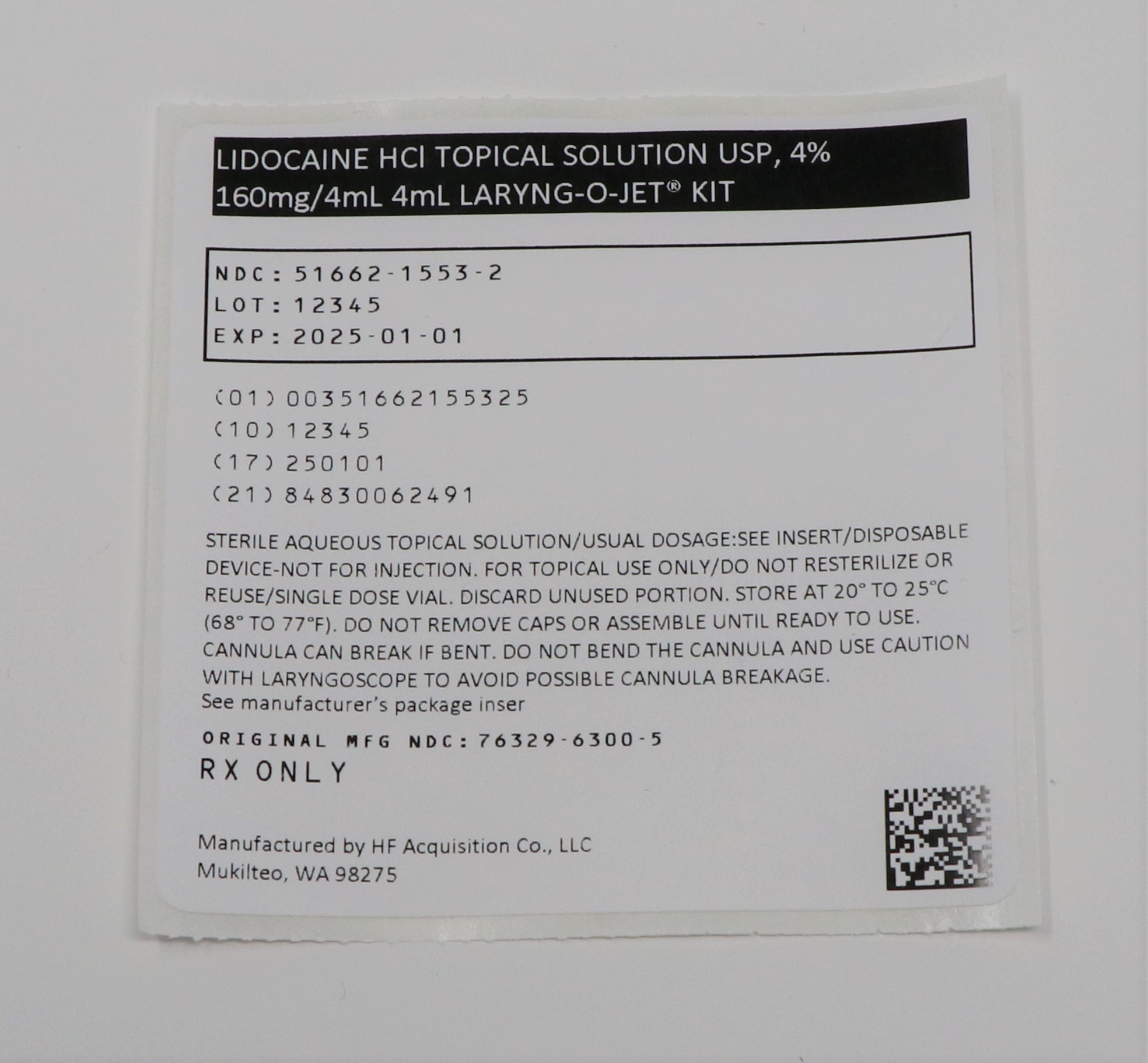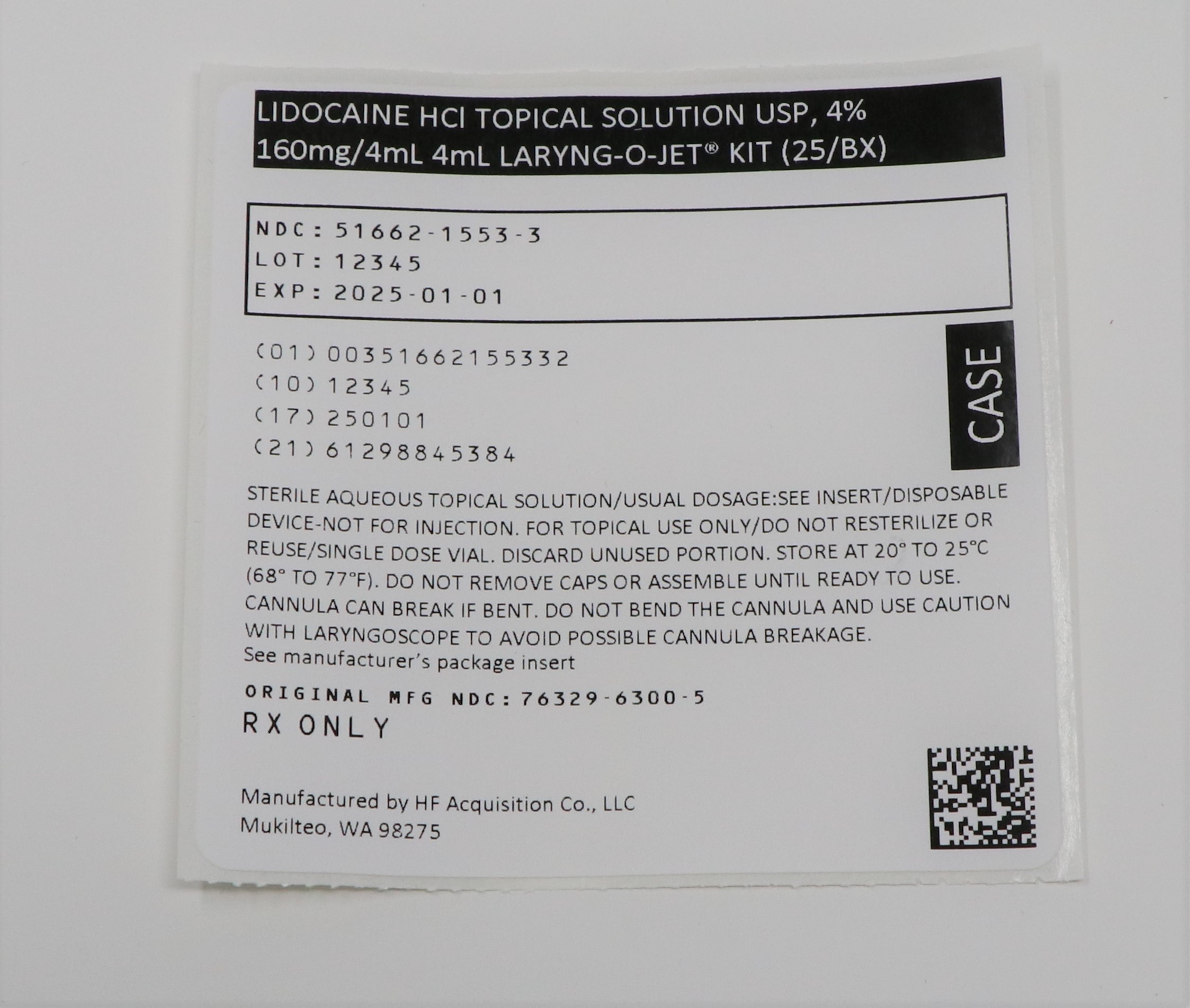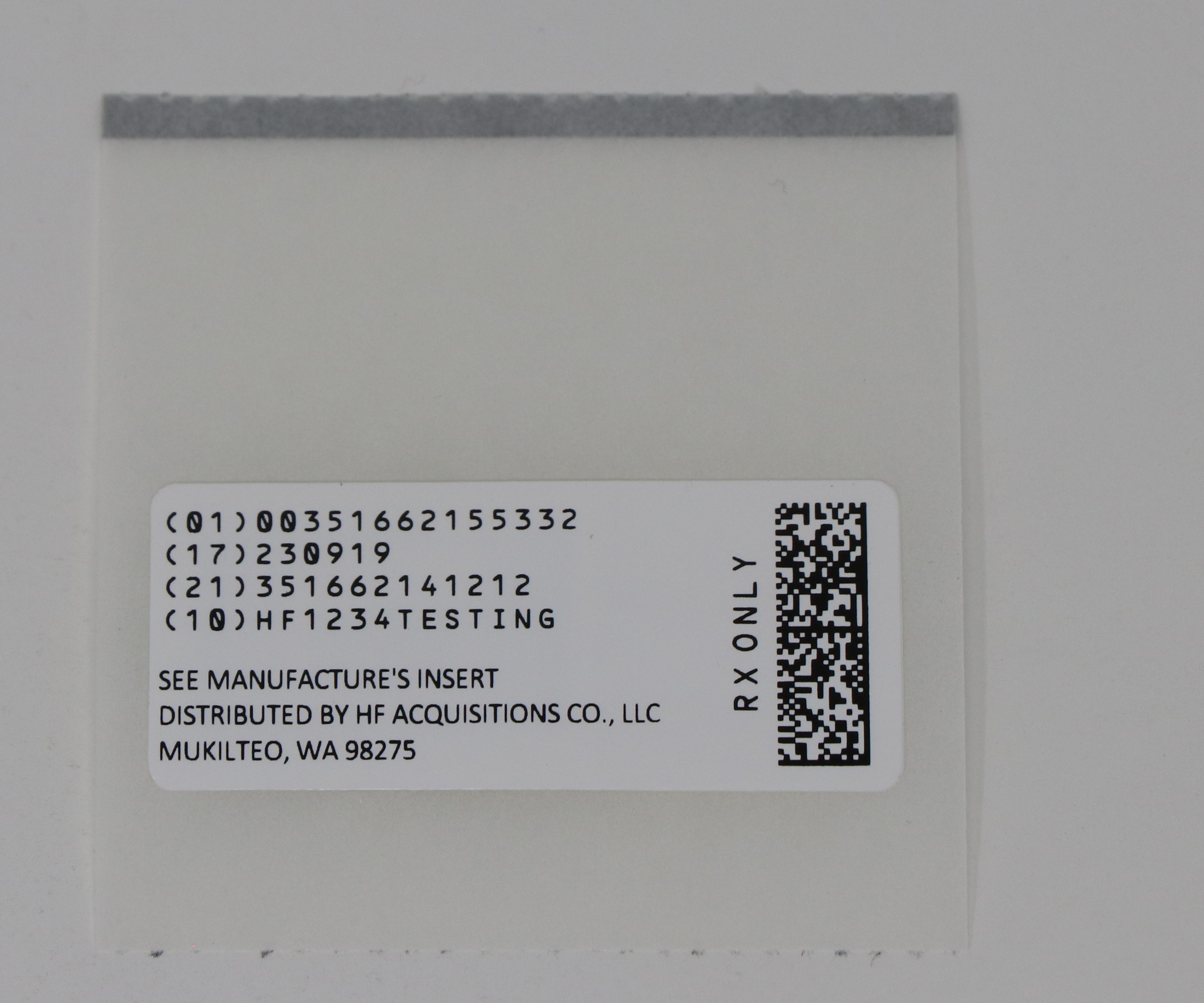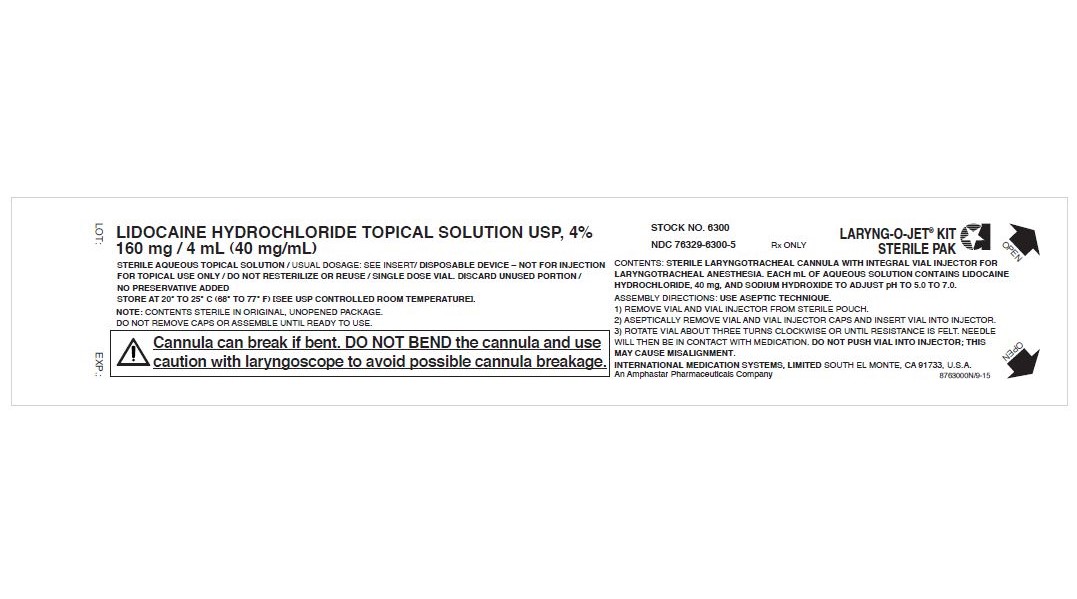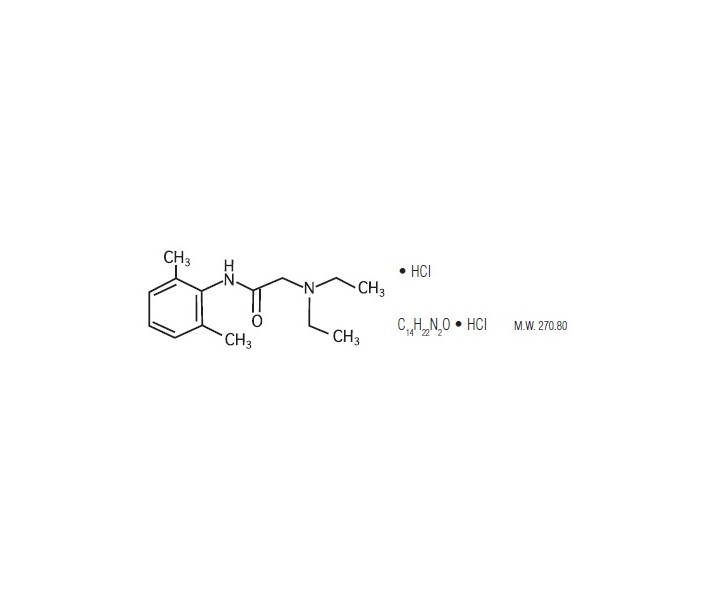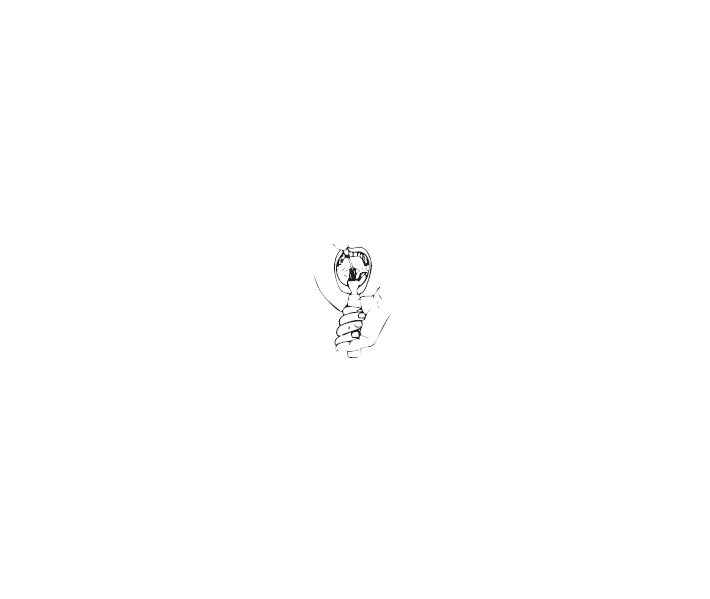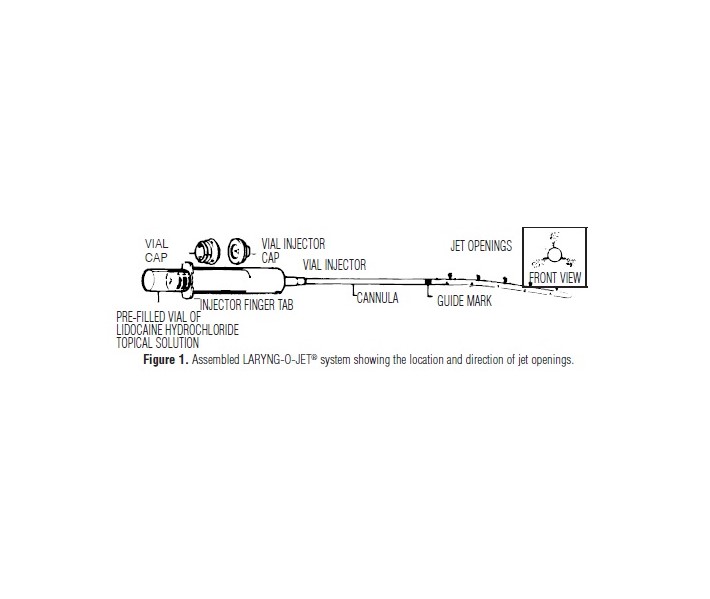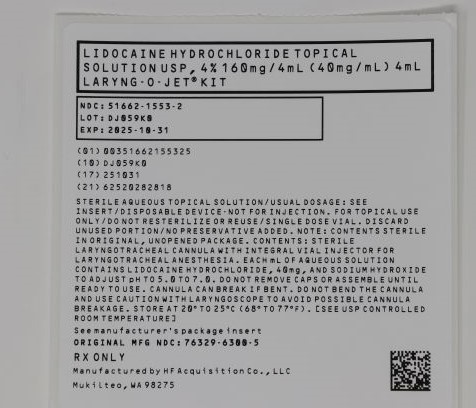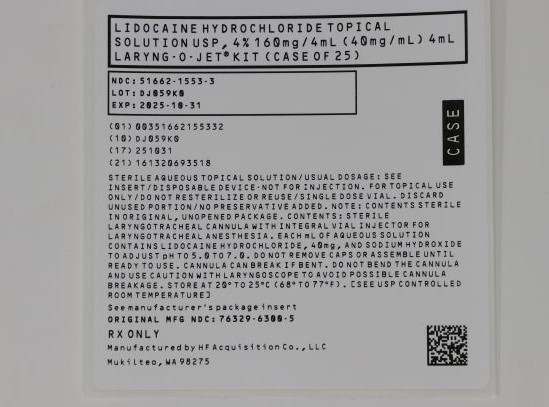 DRUG LABEL: LIDOCAINE HCl
NDC: 51662-1553 | Form: SOLUTION
Manufacturer: HF Acquisition Co LLC, DBA HealthFirst
Category: prescription | Type: HUMAN PRESCRIPTION DRUG LABEL
Date: 20240128

ACTIVE INGREDIENTS: LIDOCAINE HYDROCHLORIDE 40 mg/1 mL
INACTIVE INGREDIENTS: SODIUM HYDROXIDE; HYDROCHLORIC ACID

LIDOCAINE HCl TOPICAL SOLUTION USP, 4% 160mg/4mL 4mL LARYNG-O-JET® KIT

DESCRIPTION

Lidocaine HCI Topical Solution USP, 4% is a sterile, aqueous solution containing a local anesthetic agent and is administered topically.

Lidocaine hydrochloride is designated chemically as acetamide, 2-(diethylamino)-N-(2, 6-dimethylphenyl)-monohydrochloride, with the following structural formula:

Composition of Lidocaine HCI 4% Topical Solution: Each mL of aqueous solution contains lidocaine HCI, 40 mg, and sodium hydroxide and/or hydrochloric acid to adjust pH to 5.0 to 7.0. No preservative is added since all or part of the contents of the syringe unit is administered as a single dose and the unit should not be re-used.

CLINICAL PHARMACOLOGY

Mechanism of Action: Lidocaine stabilizes the neuronal membrane by inhibiting the ionic fluxes required for the initiation and conduction of impulses, thereby effecting local anesthetic action. The onset of action is rapid.

Hemodynamics: Excessive blood levels may cause changes in cardiac output, total peripheral resistance, and mean arterial pressure. These changes may be attributable to a direct depressant effect of the local anesthetic agent on various components of the cardiovascular system. The net effect is normally a modest hypotension when the recommended dosages are not exceeded.

Pharmacokinetics and Metabolism: Lidocaine may be absorbed following topical administration to mucous membranes, its rate and extent of absorption depending upon concentration and total dose administered, the specific site of application, and duration of exposure. In general, the rate of absorption of local anesthetic agents following topical application occurs most rapidly after intratracheal administration. Lidocaine is also well-absorbed from the gastrointestinal tract, but little intact drug appears in the circulation because of biotransformation in the liver.

Lidocaine is metabolized rapidly by the liver, and metabolites and unchanged drug are excreted by the kidneys. Biotransformation includes oxidative N-dealkylation, ring hydroxylation, cleavage of the amide linkage, and conjugation. N-dealkylation,a major pathway of biotransformation, yields the metabolites monoethylglycinexylidide and glycinexylidide. The pharmacological/toxicological actions of these metabolites are similar to, but less potent than those of lidocaine. Approximately 90% of lidocaine administered is excreted in the form of various metabolites, and less than 10% is excreted unchanged. The primary metabolite in urine is a conjugate of 4-hydroxy-2,6-dimethylaniline.

Studies have shown that peak blood levels of lidocaine may occur as early as 5 and as late as 30 minutes after endotracheal administration of a 4% lidocaine HCI solution.

The plasma binding of lidocaine is dependent on drug concentration, and the fraction bound decreases with increasing concentration. At concentrations of 1 to 4 μg of free base per mL, 60 to 80 percent of lidocaine is protein bound. Binding is also dependent on the plasma concentration of the alpha-1-acid glycoprotein.

Lidocaine crosses the blood-brain and placental barriers, presumably by passive diffusion.

Studies of lidocaine metabolism following intravenous bolus injections have shown that the elimination half-life of this agent is typically 1.5 to 2 hours. Because of the rapid rate at which lidocaine is metabolized, any condition that affects liver function may alter lidocaine kinetics. The half-life may be prolonged two-fold or more in patients with liver dysfunction. Renal dysfunction does not affect lidocaine kinetics but may increase the accumulation of metabolites.

Factors such as acidosis and the use of CNS stimulants and depressants affect the CNS levels of lidocaine required to produce overt systemic effects. Objective adverse manifestations become increasingly apparent with increasing venous plasmalevels above 6 μg free base per mL. In the rhesus monkey arterial blood levels of 18-21μg/mL have been shown to be threshold for convulsive activity.

INDICATIONS & USAGE

Lidocaine HCI Topical Solution, 4% is indicated for the production of topical anesthesia of the mucous membranes of the respiratory tract.

CONTRAINDICATIONS

Lidocaine is contraindicated in patients with a known history of hypersensitivity to local anesthetics of the amide type.

WARNINGS

LIDOCAINE HCI TOPICAL SOLUTION SHOULD BE EMPLOYED ONLY BY CLINICIANS WHO ARE WELL VERSED IN DIAGNOSIS AND MANAGEMENT OF DOSE-RELATED TOXICITY AND OTHER ACUTE EMERGENCIES THAT MIGHT ARISE AND THEN ONLY AFTER ENSURING THE IMMEDIATE AVAILABILITY OF OXYGEN, OTHER RESUSCITATIVE DRUGS, CARDIOPULMONARY EQUIPMENT, AND THE PERSONNEL NEEDED FOR PROPER MANAGEMENT OF TOXIC REACTIONS AND RELATED EMERGENCIES. (See also “ ADVERSE REACTIONS” and “ PRECAUTIONS.”) DELAY IN PROPER MANAGEMENT OF DOSE-RELATED TOXICITY, UNDERVENTILATION FROM ANY CAUSE AND/OR ALTERED SENSITIVITY MAY LEAD TO THE DEVELOPMENT OF ACIDOSIS, CARDIAC ARREST AND, POSSIBLY, DEATH.

Lidocaine HCI Topical Solution should be used with extreme caution if there is sepsis or severely traumatized mucosa in the area of application, since under such conditions there is the potential for rapid systemic absorption.

PRECAUTIONS

General: The pre-attached curved cannula is flexible but not unbreakable. Do not bend or manipulate prior to or during use, or use in conjunction with any device other than a laryngoscope. Cannula tip breakage during intratracheal anesthesia requires the tip be manually removed, prolonging anesthesia and adding additional procedural risks.

The safety and effectiveness of lidocaine depend on proper dosage, correct technique, adequate precautions, and readiness for emergencies. Resuscitative equipment, oxygen and other resuscitative drugs should be available for immediate use. (See “ WARNINGS” and “ ADVERSE REACTIONS”.) The lowest dosage that results in effective anesthesia should be used to avoid high plasma levels and serious adverse effects. Repeated doses of lidocaine may cause significant increases in blood levels with each repeated dose because of slow accumulation of the drug or its metabolites. Tolerance to elevated blood levels varies with the status of the patient. Debilitated, elderly patients, acutely ill patients, and children should be given reduced doses commensurate with their age and physical status. Lidocaine should also be used with caution in patients with severe shock or heart block.

Careful and constant monitoring of cardiovascular and respiratory (adequacy of ventilation) vital signs and the patient’s state of consciousness should be accomplished after each local anesthetic injection. It should be kept in mind at such times that restlessness, anxiety, tinnitus, dizziness, blurred vision, tremors, depression or drowsiness may be early warning signs of central nervous system toxicity.

Since amide-type local anesthetics are metabolized by the liver, Lidocaine HCI Topical Solution should be used with caution in patients with hepatic disease. Patients with severe hepatic disease, because of their inability to metabolize local anesthetics normally, are at a greater risk of developing toxic plasma concentrations. Lidocaine HCI Topical Solution should also be used with caution in patients with impaired cardiovascular function since they may be less able to compensate for functional changes associated with the prolongation of A-V conduction produced by these drugs.

Many drugs used during the conduct of anesthesia are considered potential triggering agents for familial malignant hyperthermia. Since it is not known whether amide-type local anesthetics may trigger this reaction and since the need for supplemental general anesthesia cannot be predicted in advance, it is suggested that a standard protocol for management should be available. Early unexplained signs of tachycardia, tachypnea, labile blood pressure and metabolic acidosis may precede temperature elevation. Successful outcome is dependent on early diagnosis, prompt discontinuance of the suspect triggering agent(s) and institution of treatment, including oxygen therapy, indicated supportive measures and dantrolene (consult dantrolene sodium intravenous package insert before using).

Lidocaine should be used with caution in persons with known drug sensitivities. Patients allergic to para-amino-benzoic acid derivatives (procaine, tetracaine, benzocaine, etc.) have not shown cross sensitivity to lidocaine.

Information for Patients: When topical anesthetics are used in the mouth, the patient should be aware that the production of topical anesthesia may impair swallowing and thus enhance the danger of aspiration. For this reason, food should not be ingestedfor 60 minutes following use of local anesthetic preparations in the mouth or throat area. This is particularly important in children because of their frequency of eating.

Numbness of the tongue or buccal mucosa may enhance the danger of unintentional biting trauma. Food and chewing gum should not be used while the mouth or throat area is anesthetized.

Carcinogenesis, Mutagenesis, Impairment of Fertility: Studies of lidocaine in animals to evaluate the carcinogenic and mutagenic potential or the effect on fertility have not been conducted.

Use in Pregnancy: Teratogenic Effects: Pregnancy Category B

Reproduction studies have been performed in rats at doses up to 6.6 times the human dose and have revealed no evidence of harm to the fetus caused by lidocaine. There are, however, no adequate and well-controlled studies in pregnant women. Animal reproduction studies are not always predictive of human response. General consideration should be given to this fact before administering lidocaine to women of childbearing potential, especially during early pregnancy when maximum organogenesis takes place.

Labor and delivery: Lidocaine is not contraindicated in labor and delivery. Should Lidocaine HCI Topical Solution be used concomitantly with other products containing lidocaine, the total dose contributed by all formulations must be kept in mind.

Nursing mothers: It is not known whether this drug is excreted in human milk. Because many drugs are excreted in human milk, caution should be exercised when lidocaine is administered to a nursing woman.

Pediatric use: Dosages in children should be reduced, commensurate with age and body weight. See “ DOSAGE AND ADMINISTRATION.”

ADVERSE REACTIONS

Adverse experiences following the administration of lidocaine are similar in nature to those observed with other amide local anesthetic agents. These adverse experiences are, in general, dose-related and may result from high plasma levels caused by excessive dosage or rapid absorption, or may result from a hypersensitivity, idiosyncrasy or diminished tolerance on the part of the patient. Serious adverse experiences are generally systemic in nature.

The following types are those most commonly reported:

Central Nervous System: CNS manifestations are excitatory and/or depressant and may be characterized by lightheadedness, nervousness, apprehension, euphoria, confusion, dizziness, drowsiness, tinnitus, blurred or double vision, vomiting, sensations of heat, cold or numbness, twitching, tremors, convulsions, unconsciousness, respiratory depression and arrest. The excitatory manifestations may be very brief or may not occur at all, in which case the first manifestation of toxicity may be drowsiness merging into unconsciousness and respiratory arrest.

Drowsiness following the administration of lidocaine is usually an early sign of a high blood level of the drug and may occur as a consequence of rapid absorption.

Cardiovascular System: Cardiovascular manifestations are usually depressant and are characterized by bradycardia, hypotension, and cardiovascular collapse, which may lead to cardiac arrest.

Allergic: Allergic reactions are characterized by cutaneous lesions, urticaria, edema or anaphylactoid reactions. Allergic reactions as a result of sensitivity to lidocaine are extremely rare and, if they occur, should be managed by conventional means. The detection of sensitivity by skin testing is of doubtful value.

Neurologic: The incidences of adverse reactions associated with the use of local anesthetics may be related to the total dose of local anesthetic administered and are also dependent upon the particular drug used, the route of administration and the physicalstatus of the patient.

OVERDOSAGE

Acute emergencies from local anesthetics are generally related to high plasma levels encountered during therapeutic use of local anesthetics. See “ ADVERSE REACTIONS”, “ WARNINGS” and “ PRECAUTIONS.”

The intravenous LD50 of lidocaine HCl in female mice is 26 (21-31) mg/kg and the subcutaneous LD50 is 264 (203-304) mg/kg.
Management of Local Anesthetic Emergencies: The first consideration is prevention, best accomplished by careful and constant monitoring of cardiovascular and respiratory vital signs and the patient’s state of consciousness after each local anestheticadministration. At the first sign of change, oxygen should be administered.

The first step in the management of convulsions consists of immediate attention to the maintenance of a patent airway and assisted or controlled ventilation with oxygen and a delivery system capable of permitting immediate positive airway pressure by mask. Immediately after the institution of these ventilatory measures, the adequacy of the circulation should be evaluated, keeping in mind that drugs used to treat convulsions sometimes depress the circulation when administered. Should convulsions persist despite adequate respiratory support, and if the status of the circulation permits, small increments of an ultra-short acting barbiturate (such as thiopental or thiamylal) or a benzodiazepine (such as diazepam) may be administered intravenously. The clinician should be familiar, prior to use of local anesthetics, with these anticonvulsant drugs. Supportive treatment of circulatorydepression may require administration of intravenous fluids and, when appropriate, a vasopressor as directed by the clinical situation (e.g., ephedrine).

If not treated immediately, both convulsions and cardiovascular depression can result in hypoxia, acidosis, bradycardia, arrhythmias and cardiac arrest. If cardiac arrest should occur, standard cardiopulmonary resuscitative measures should be instituted.

Endotracheal intubation, employing drugs and techniques familiar to the clinician, may be indicated, after initial administration of oxygen by mask, if difficulty is encountered in the maintenance of a patent airway or if prolonged ventilatory support (assisted or controlled) is indicated.

Dialysis is of negligible value in the treatment of acute overdosage with lidocaine.

DOSAGE & ADMINISTRATION

When Lidocaine HCI Topical Solution is used concomitantly with other products containing lidocaine, the total dose contributed by all formulations must be kept in mind.

The dosage varies and depends upon the area to be anesthetized, vascularity of the tissues, individual tolerance and the technique of anesthesia. The lowest dosage needed to provide effective anesthesia should be administered. Dosages should be reduced for children and for elderly and debilitated patients.

Although the incidence of adverse effects with Lidocaine HCI Topical Solution is quite low, caution should be exercised, particularly when employing large volumes and concentrations of Lidocaine HCI Topical Solution since the incidence of adverse effects is directly proportional to the total dose of local anesthetic agent administered. For specific techniques and procedures refer to standard textbooks. The dosages below are for normal, healthy adults.

Topical Application: For laryngoscopy, bronchoscopy and endotracheal intubation, the pharynx may be sprayed with 1-5 mL (40-200 mg lidocaine HCI), i.e., 0.6-3 mg/kg or 0.3-1.5 mg/lb body weight. For local anesthesia by the transtracheal route, it may be occasionally necessary to spray the pharynx by oropharyngeal spray to achieve complete analgesia.

Maximum Recommended Dosages:

Normal Healthy Adults:The maximum recommended dose of Lidocaine HCI Topical Solution, should be such that the dose of lidocaine HCI is kept below 300 mg and in any case should not exceed 4.5 mg/kg (2 mg/lb) body weight.

Children: It is difficult to recommend a maximum dose of any drug for children since this varies as a function of age and weight. For children of less than ten years who have a normal lean body mass and normal body development, the maximum dose may be determined by the application of one of the standard pediatric drug formulas (e.g. Clark’s rule). For example, in a child of five years weighing 50 Ibs., the dose of lidocaine HCI should not exceed 75-100 mg when calculated according to Clark’s rule. The amount of Lidocaine HCI Topical Solution administered should be such that the dose of lidocaine is kept below 300 mg and in any case should not exceed 4.5 mg/kg (2.0 mg/lb) of body weight.

Directions for Use

DESCRIPTION

The LARYNG-O-JET® is a disposable kit for producing rapid, effective topical anesthesia of the interior of the larynx and trachea. The kit contains (1) a sterile, anatomically-curved plastic cannula with attached vial injector, and (2) a single-dose vial prefilled with 4 mL of a 4% sterile aqueous solution of lidocaine hydrochloride. Medication, cannula and fluid pathway are sterile in original, unopened package. The kit is designed for one-time use only. After use, it may be discarded without disassembly.

USE

The LARYNG-O-JET® Kit is used to instill a jet spray of lidocaine hydrochloride topical solution into the interior of the larynx and trachea for local anesthesia in the unconscious patient just prior to endotracheal intubation. This form of application also is effective as a final stage of topical anesthesia in the conscious patient (after initial use of an atomizer spray or other appropriate technique for applying topical anesthetic to the pharynx and epiglottis) prior to laryngeal or tracheobronchial endoscopic procedures.

DIRECTIONS

Use Aseptic Technique

DO NOT ASSEMBLE UNTIL READY TO USE

IMPORTANT:

Cannula can break if bent. DO NOT BEND the cannula and use caution with laryngoscope to avoid possible cannula breakage.
Cases of cannula tip breakage during or immediately prior to use have been reported. Cannula tip breakage is thought to be related to user
manipulation prior to or during use, or with concomitant use with other intubation devices. (see PRECAUTIONS).
Use of the LARYNG-O-JET® Kit requires strict observance of precautions appropriate to use of topical anesthesia in the respiratory tract.

For Use Prior to Intubation During Anesthesia Induction (Unconscious Patient):

1. Open kit following peel pouch directions.
2. Remove vial and vial injector from bag.
3. Aseptically remove vial and vial injector caps and insert vial into injector.
4. Rotate vial about three turns clockwise or until resistance is felt. DO NOT PUSH VIAL INTO INJECTOR; THIS MAY CAUSE MISALIGNMENT. Needle will then be in contact with medication (Fig. 1). Assembled unit should remain sterile in field until laryngoscopy has been completed.
*The pre-attached curved cannula is flexible but not unbreakable. Cannula can break if bent. DO NOT BEND OR MANIPULATE PRIOR TO USE to avoid possible cannula breakage.
5. Before instillation, manually ventilate the patient with 5 or 6 deep breaths of 100% oxygen (denitrogenate with at least 5 minutes of high flow semi-closed 100% oxygen administration in patients with low cardio-respiratory, circulatory, or hematologic reserve).
6. Predetermine dose (volume) of anesthetic to be instilled and expel excess solution.
7. After hypnosis and muscle relaxation have developed fully and oxygenation has been accomplished as above, perform laryngoscopy in conventional manner. See Fig. 2.

Figure 2. Laryngoscopist's view showing cannula in place in adult larynx and trachea, with black guide mark just proximal to cords.

8. Hold injector in manner of holding a pen, and insert tip of cannula between vocal cords and into trachea to the proper depth for instillation of local anesthetic. The black guide mark is positioned just proximal to vocal cords. At this depth, interior of larynx will be bathed with anesthetic solution from upper jet orifices and entire tracheal wall by lower jet openings. (NOTE: Black mark on cannula shaft indicates approximate depth for insertion in most normal patients without touching carina with distal tip.) Caution and gentleness during insertion should be observed and the cannula advanced a proportionately shorter distance in those persons suspected of having a high tracheal bifurcation or tracheobronchial anomaly. USE CAUTION WITH LARYNGOSCOPE TO A VOID POSSIBLE CANNULA BREAKAGE.
9. With cannula at proper depth, depress syringe plunger rapidly to produce a jet-like instillation for bathing walls of larynx and trachea. NOTE: Depression of syringe plunger too slowly may fail to eject solution with sufficient velocity to reach all parts of the larynx and trachea.
10. Withdraw unit and discard.
11. Proceed with intubation.

For Use in Endoscopic Procedures to Supplement Initial Atomizer Spray of Local Anesthetic (Conscious Patient):

1. Predetermine dose and assemble unit as in steps 1, 2, 3, 4 and 6 (above).
2. Before instillation apply an initial local anesthetic to the pharynx and epiglottis using an atomizer spray or other appropriate technique.
3. Follow steps 8, 9 and 10 (above) for instillation.
4. Proceed with desired laryngeal or tracheobronchial endoscopy.

HOW SUPPLIED

In unit use packages containing one sterile disposable laryngotracheal cannula with attached vial injector, and one disposable single dose vial prefilled with sterile, aqueous solution of lidocaine hydrochloride.

NDC 51662-1553-2 LIDOCAINE HCl TOPICAL SOLUTION USP, 4% 160mg/4mL 4mL LARYNG-O-JET® KIT, 1 per Pouch

NDC 51662-1553-3 LIDOCAINE HCl TOPICAL SOLUTION USP, 4% 160mg/4mL 4mL LARYNG-O-JET® KIT, 1 per Pouch, 25 per Case

HF Acquisition Co LLC, DBA HealthFirst
11629 49th Pl W.

Mukilteo, WA 98275

Store at 20° to 25°C (68° to 77°F)[see USP Controlled Room Tempertaure].

PRINCIPAL DISPLAY PANEL - 51662-1553-2, POUCH Updated September 2022

51662-1553-2, Updated Pouch Label September 2022

PRINCIPAL DISPLAY PANEL - 51662-1553-3, Case Labeling Updated September 2022

51662-1553-3, Updated Case Labeling